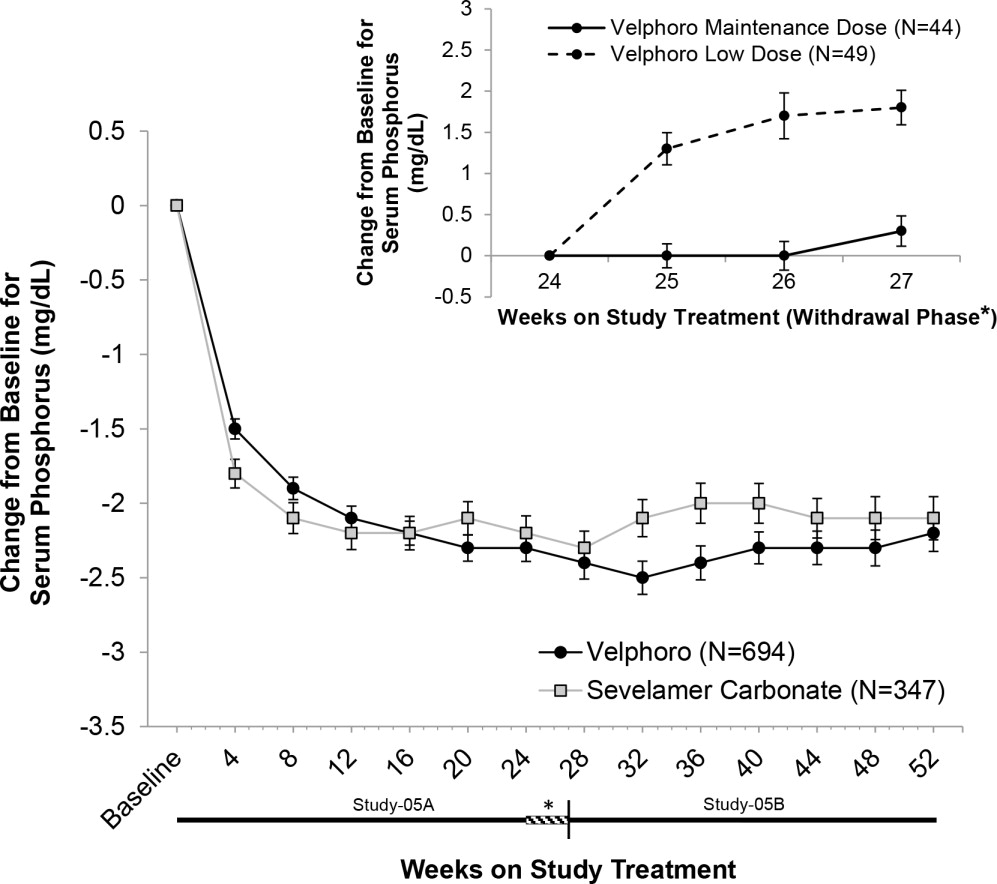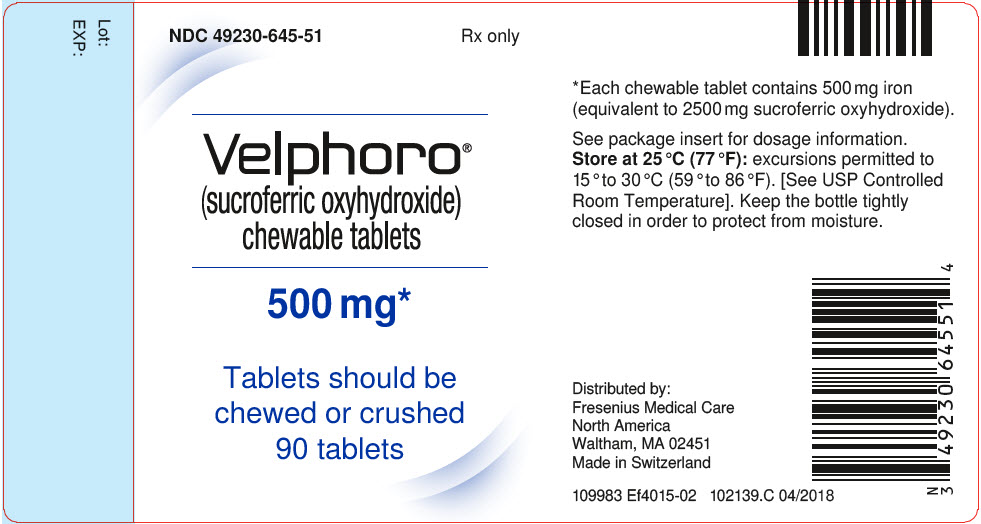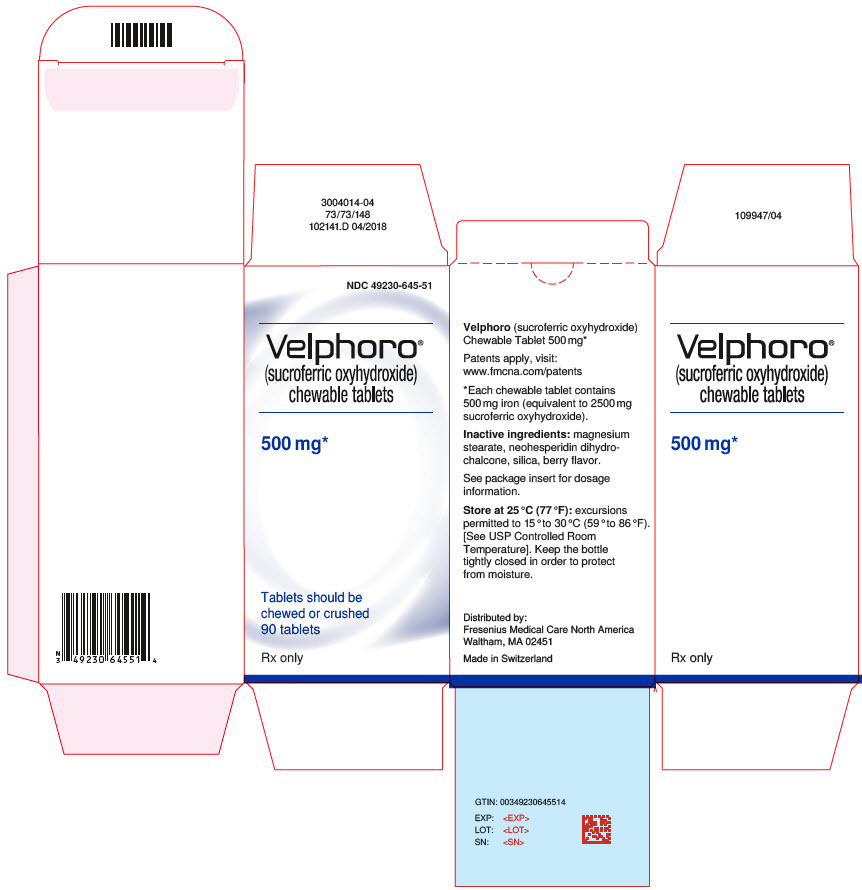 DRUG LABEL: Velphoro
NDC: 49230-645 | Form: TABLET, CHEWABLE
Manufacturer: Fresenius Medical Care Renal Therapies Group, LLC
Category: prescription | Type: HUMAN PRESCRIPTION DRUG LABEL
Date: 20251118

ACTIVE INGREDIENTS: FERRIC OXYHYDROXIDE
 500 mg/1 1

HIGHLIGHTS OF PRESCRIBING INFORMATION

These highlights do not include all the information needed to use VELPHORO®safely and effectively. See full prescribing information for VELPHORO®.
VELPHORO®(sucroferric oxyhydroxide) chewable tablet for oral use
Initial U.S. Approval: 2013

RECENT MAJOR CHANGES

Indications and Usage (1) | 7/2024
Dosage and Administration (2.1) | 7/2024

1 INDICATIONS AND USAGE

Velphoro is a phosphate binder indicated for the control of serum phosphorus levels in adult and pediatric patients 9 years of age and older with chronic kidney disease on dialysis. (1)

2 DOSAGE AND ADMINISTRATION

- Chew or crush Velphoro tablets, do not swallow whole. (2.2)
- The recommended starting dose for adults and pediatric patients 12 years of age and older is one 500 mg tablet three times daily with meals. (2.1)
- The recommended starting dose for pediatric patients 9 to <12 years of age is one 500 mg tablet two times daily with meals. (2.1)
- Adjust dosage by one 500 mg tablet per day as needed until an acceptable serum phosphorus level is reached, with regular monitoring afterwards. Titrate as often as weekly. (2.1)

3 DOSAGE FORMS AND STRENGTHS

- Velphoro chewable tablet 500 mg (3)

4 CONTRAINDICATIONS

- None (4)

5 WARNINGS AND PRECAUTIONS

- Patients with peritonitis during peritoneal dialysis, significant gastric or hepatic disorders, history of recent major gastrointestinal surgery, or with a history of hemochromatosis or other diseases with iron accumulation have not been included in clinical studies with Velphoro. Monitor effect and iron homeostasis in such patients. (5.1)

6 ADVERSE REACTIONS

- The most common adverse drug reactions to Velphoro chewable tablets in clinical trials were discolored feces (12%) and diarrhea (6%). (6.1)

To report SUSPECTED ADVERSE REACTIONS, contact Fresenius Medical Care North America at 1-800-323-5188 or FDA at 1-800-FDA-1088 orwww.fda.gov/medwatch.

7 DRUG INTERACTIONS

- Velphoro can be administered concomitantly with oral calcitriol, ciprofloxacin, digoxin, enalapril, furosemide, HMG‑CoA reductase inhibitors, hydrochlorothiazide, losartan, metoprolol, nifedipine, omeprazole, quinidine and warfarin. (7)
- Take acetylsalicylic acid, cephalexin and doxycycline at least 1 hour before Velphoro. (7)
- Take levothyroxine at least 4 hours before Velphoro. (7)
- For oral medications not listed above where a reduction of bioavailability would be clinically significant consider separation of the timing of administration. Consider monitoring clinical responses or blood levels of the concomitant medication (7)

FULL PRESCRIBING INFORMATION

1 INDICATIONS AND USAGE

Velphoro is indicated for the control of serum phosphorus levels in adults and pediatric patients 9 years of age and older with chronic kidney disease (CKD) on dialysis.

2 DOSAGE AND ADMINISTRATION

2.1 General Dosing Information

The recommended starting dose of Velphoro in adults and pediatric patients 12 years of age and older is one 500 mg tablet three times daily with meals. The recommended starting dose of Velphoro in pediatric patients 9 to <12 years of age is one 500 mg tablet two times daily with meals.

Monitor serum phosphorus levels and titrate the dose of Velphoro in decrements or increments of one 500 mg tablet per day as needed until an acceptable serum phosphorus level is reached, with regular monitoring afterwards. Titrate as often as weekly. If the recommended daily dose cannot be divided equally among meals, administer the larger dose with the largest meal of the day.

In clinical studies, on average, adult patients and pediatric patients 12 years of age and older required 1,500 mg to 2,000 mg (3 to 4 tablets) a day to control serum phosphorus levels; pediatric patients 9 to <12 years of age required on average 1,500 mg (3 tablets) to control serum phosphorus levels. Daily doses as high as 3,000 mg per day have been studied in adults and pediatric patients 9 years of age and older.

2.2 Administration

Velphoro chewable tablets should be chewed or crushed. Do not swallow whole.

Velphoro chewable tablets must be administered with meals.

If one or more doses of Velphoro are missed, the medication should be resumed with the next food intake.

3 DOSAGE FORMS AND STRENGTHS

Velphoro is supplied in a strength of 500 mg as a brown, circular, bi-planar chewable tablet embossed with “PA 500” on one side.

Each chewable tablet contains 500 mg iron (equivalent to 2,500 mg sucroferric oxyhydroxide).

4 CONTRAINDICATIONS

None.

5 WARNINGS AND PRECAUTIONS

5.1 Monitoring in Patients with Gastrointestinal Disorders or Iron Accumulation Disorders

Each chewable tablet contains 500 mg iron (equivalent to 2,500 mg sucroferric oxyhydroxide) [see Clinical Pharmacology (12.3)] . Patients with peritonitis during peritoneal dialysis, significant gastric or hepatic disorders, following major gastrointestinal (GI) surgery, or with a history of hemochromatosis or other diseases with iron accumulation have not been included in clinical studies with Velphoro.

Monitor effect and iron homeostasis in such patients.

6 ADVERSE REACTIONS

6.1 Clinical Trial Experience

Adult Patients

Because clinical trials are conducted under widely varying conditions, adverse reaction rates observed in the clinical trials of a drug cannot be directly compared to rates in the clinical trials of another drug and may not reflect the rates observed in practice.

The safety data derived from Velphoro clinical trials reflect exposure to Velphoro in 2 active-controlled clinical studies involving a total of 778 adult patients on hemodialysis and 57 adult patients on peritoneal dialysis exposed for up to 55 weeks. Dosage regimens ranged from 250 mg to 3,000 mg per day.

In a parallel design, dose-finding study of Velphoro with a treatment duration of 6 weeks in hemodialysis patients, adverse reactions for Velphoro (N=128) were similar to those reported for the active-control group (sevelamer hydrochloride) (N=26), with the exception of discolored feces (12%) which did not occur in the active-control group. Diarrhea was reported in 6% of patients treated with Velphoro. In a 55-week, open-label, active-controlled, parallel design, safety and efficacy study involving 968 hemodialysis patients and 86 peritoneal dialysis patients treated with either Velphoro (N=707 including 57 peritoneal dialysis patients) or the active-control (sevelamer carbonate) (N=348 including 29 peritoneal dialysis patients), adverse reactions occurring in more than 5% in the Velphoro group were diarrhea (24%), discolored feces (16%), and nausea (10%). The majority of diarrhea events in the Velphoro group were mild and transient, occurring soon after initiation of treatment, and resolving with continued treatment. Adverse reactions occurred at similar rates in hemodialysis and peritoneal dialysis patients. The most common adverse reactions (>1%) leading to withdrawal were diarrhea (4%), product taste abnormal (2%), and nausea (2%).

Pediatric Patients

In an open-label, randomized study, with a 10-week dose titration period and 24-week safety extension, 60 patients 6 to 18 years of age received at least one dose of Velphoro, including 30 patients (50%) exposed for at least 19 weeks [see Clinical Studies (14.3)] . The safety profile of Velphoro in pediatric patients was similar to that observed in adult patients. Velphoro is not approved in pediatric patients 6 years to less than 9 years of age because of the lack of an appropriate dosage strength.

6.2 Postmarketing Experience

The following adverse reactions have been identified during post-approval use of Velphoro that are not included in other sections of labeling. Because these reactions are reported voluntarily from a population of uncertain size, it is not always possible to reliably estimate their frequency or establish a causal relationship to drug exposure.

Gastrointestinal Disorders: tooth discoloration

Skin and Subcutaneous Tissue Disorders: rash

7 DRUG INTERACTIONS

Table 1 Oral drugs that can be administered concomitantly with Velphoro
Calcitriol
Ciprofloxacin
Digoxin
Enalapril
Furosemide
HMG-CoA reductase inhibitors
Hydrochlorothiazide
Losartan
Metoprolol
Nifedipine
Omeprazole
Quinidine
Warfarin
Oral drugs that are to be separated from Velphoro
 | Dosing Recommendations
Doxycycline Acetylsalicylic acid Cephalexin | Take at least 1 hour before Velphoro.
Levothyroxine | Take at least 4 hours before Velphoro

Oral medications not listed in Table 1

There are no empirical data on avoiding drug interactions between Velphoro and most concomitant oral drugs. For oral medications where a reduction in the bioavailability of that medication would have a clinically significant effect on its safety or efficacy, consider separating the administration of the two drugs. The necessary separation depends upon the absorption characteristics of the medication concomitantly administered, such as the time to reach peak systemic levels and whether the drug is an immediate-release or an extended-release product. Where possible, consider monitoring for clinical response and/or blood levels of concomitant medications that have a narrow therapeutic range.

8 USE IN SPECIFIC POPULATIONS

8.1 Pregnancy

Velphoro is not systemically absorbed following oral administration and maternal use is not expected to result in fetal exposure to the drug.

Data

Animal Data

In pregnant rats given up to 800 mg/kg/day Velphoro by oral gavage from Days 6 to 17 post-mating, no embryo-fetal development toxicity was observed. This dose corresponds to 16 times the maximum recommended clinical dose.

In pregnant rabbits given 50, 100 or 200 mg/kg/day Velphoro by oral gavage, from Days 6 to 19 post-mating, the number of fetuses with incomplete/unossified epiphyses and metacarpals/phalanges was increased at the highest dose (corresponding to 4 times the recommended maximum clinical dose). Litter parameters were not adversely affected.

In pregnant rats given Velphoro at 100, 280, or 800 mg/kg/day by oral gavage from Day 6 post-mating to lactation Day 20, offspring body weight gain was lower at age 5-13 weeks and neuromuscular function was delayed at the dose of 800 mg/kg/day. This dose represented 16 times the maximum recommended clinical dose.

8.2 Lactation

Velphoro is not absorbed systemically following oral administration and breastfeeding is not expected to result in exposure of the child to Velphoro.

8.4 Pediatric Use

Velphoro is indicated for the control of serum phosphorus levels in pediatric patients 9 years of age and older with CKD on dialysis. Use of Velphoro for this indication is supported by evidence from an adequate and well-controlled study in adults, with additional pharmacodynamic and safety data in pediatric patients with advanced CKD (an estimated glomerular filtration rate <30 mL/min/1.73 m^2or CKD on dialysis) [see Adverse Reactions (6.1) and Clinical Studies (14.3)] .

The safety and effectiveness of Velphoro have been established for the control of serum phosphorus levels in pediatric patients 6 years to less than 9 years of age with CKD on dialysis, but Velphoro is not approved in pediatric patients 6 years to less than 9 years of age because of the lack of an appropriate dosage strength.

The safety and effectiveness of Velphoro have not been established in pediatric patients younger than 6 years of age. Although the study included six patients 2 to <6 years of age who received Velphoro, based on the available data, it is unclear whether the dosing regimen that was evaluated is effective in reducing serum phosphorus in this age group.

Velphoro has not been studied in pediatric patients below 2 years of age.

8.5 Geriatric Use

Of the total number of subjects in two active-controlled clinical studies of Velphoro (N=835), 29.7% (n=248) were 65 and over, while 8.7% (n=73) were aged 75 years and over. No overall differences in safety or effectiveness were observed between these subjects and younger subjects.

10 OVERDOSAGE

There are no reports of overdosage with Velphoro in patients. Since the absorption of iron from Velphoro is low [see Clinical Pharmacology (12.3)] , the risk of systemic iron toxicity is low. Hypophosphatemia should be treated by standard clinical practice.

Velphoro has been studied in doses up to 3,000 mg per day.

11 DESCRIPTION

The Velphoro drug substance is a mixture of polynuclear iron(III)-oxyhydroxide, sucrose, and starches. The active moiety of Velphoro, polynuclear iron(III)-oxyhydroxide, is practically insoluble and cannot be absorbed.

Velphoro chewable tablets for oral use are brown, circular, bi-planar, and are embossed with “PA 500” on 1 side. Each tablet of Velphoro contains 500 mg iron (in 2,500 mg sucroferric oxyhydroxide). One tablet is equivalent to approximately 1.4 g of carbohydrates (750 mg sucrose and 700 mg starches as potato starch and pregelatinized maize starch). The inactive ingredients are berry flavor, neohesperidin dihydrochalcone, magnesium stearate, and silica (colloidal, anhydrous).

12 CLINICAL PHARMACOLOGY

12.1 Mechanism of Action

In the aqueous environment of the GI tract, phosphate binding takes place by ligand exchange between hydroxyl groups and/or water in sucroferric oxyhydroxide and the phosphate in the diet. The bound phosphate is eliminated with feces.

Both serum phosphorus levels and calcium-phosphorus product levels are reduced as a consequence of the reduced dietary phosphate absorption.

12.2 Pharmacodynamics

In vitrostudies have demonstrated a robust phosphate binding capacity of Velphoro over the physiologically relevant pH range of the GI tract (1.2-7.5). The phosphate binding capacity of Velphoro peaked at pH 2.5, resulting in 96% of the available phosphate being adsorbed (phosphorus:iron concentration ratio 0.4:1).

12.3 Pharmacokinetics

The active moiety of Velphoro, polynuclear iron (III)-oxyhydroxide (pn-FeOOH), is practically insoluble in water and therefore not absorbed and not metabolized. Its degradation product, mononuclear iron species, can however be released from the surface of pn-FeOOH and be absorbed.

Because of the insolubility and degradation characteristics of Velphoro, no classical pharmacokinetic studies can be carried out.

The sucrose and starch components of Velphoro can be digested to glucose and fructose, and maltose and glucose, respectively. These compounds can be absorbed in the blood.

The iron uptake from radiolabeled Velphoro drug substance, 2,000 mg in 1 day, was investigated in 16 chronic kidney disease patients (8 pre-dialysis and 8 hemodialysis patients) and 8 healthy volunteers with low iron stores (serum ferritin <100 mcg/L). In healthy subjects, the median uptake of radiolabeled iron in the blood was 0.43% on Day 21. In chronic kidney disease patients, the median uptake was much less, 0.04% on Day 21.

Drug Interaction Studies

In vitro

In vitrointeractions were studied in aqueous solutions which mimic the physico-chemical conditions of the gastro-intestinal tract with or without the presence of phosphate (400 mg). The study was conducted at pH 3.0, 5.5 and 8.0 with incubation at 37°C for 6 hours.

Interaction with Velphoro was seen with the following drugs: alendronate, doxycycline, acetylsalicylic acid, cephalexin, levothyroxine, and paricalcitol.

The following drugs did not show interaction with Velphoro: ciprofloxacin, enalapril, hydrochlorothiazide, metoprolol, nifedipine, and quinidine.

In vivo

Five in vivodrug interaction studies (N=40/study) were conducted with losartan, furosemide, digoxin, omeprazole and warfarin in healthy subjects receiving 1,000 mg Velphoro 3 times a day with meals. Velphoro did not alter the systemic exposure as measured by the area under the curve (AUC) of the tested drugs when co-administered with Velphoro or given 2 hours later.

Data from the clinical studies (Study-05A and Study-05B) show that Velphoro does not affect the lipid lowering effects of HMG-CoA reductase inhibitors or the PTH lowering effect of calcitriol.

13 NONCLINICAL TOXICOLOGY

13.1 Carcinogenesis, Mutagenesis, Impairment of Fertility

Carcinogenicity studies were performed in mice and rats.

In the 2-year carcinogenicity study in mice, animals were given Velphoro by diet at doses of 250, 500 or 1,000 mg/kg/day. There was no clear evidence of a carcinogenic effect in mice. Mucosal hyperplasia, with diverticulum/cyst formation was observed in the colon and caecum of mice after 2 years treatment. In the 2-year rat carcinogenicity study, animals were given Velphoro by diet at doses of 40, 150 or 500 mg/kg/day. No statistically significantly increased incidences of tumors were found, but there were increased incidences in epithelial hyperplasia with or without submucosal inflammation in duodenum, cecum and colon at the dose of 500 mg/kg/day (10 times the maximum recommended clinical dose).

Velphoro was not mutagenic, clastogenic or DNA damaging in vitroin the Ames bacterial reverse mutation test, or in the Chinese-hamster fibroblast chromosomal aberration test, or in vivoin the rat Comet assay or peripheral blood micronucleus test.

In rats, mating performance and fertility were unaffected by Velphoro at oral doses up to 800 mg/kg/day (16 times the maximum recommended clinical dose).

14 CLINICAL STUDIES

14.1 Fixed-dose Study

In Study-03A, 154 ESRD adult patients on hemodialysis who were hyperphosphatemic (serum phosphorus >5.5 mg/dL but <7.75 mg/dL) following a 2-week phosphate binder washout period, were randomized to receive Velphoro at 250 mg/day, 1,000 mg/day, 1,500 mg/day, 2,000 mg/day, or 2,500 mg/day or active-control (sevelamer hydrochloride). Velphoro treatment was divided across meals, depending on dose. No dose titration was allowed. Within each of the groups, the serum phosphorus level at the end of treatment was compared to baseline value. Velphoro was shown to be efficacious (p≤0.016) for all doses except 250 mg/day. There were no patient-reported dose limiting treatment-emergent adverse events.

Mean changes in iron parameters (ferritin, transferrin saturation (TSAT) and transferrin) and vitamins (A, D, E and K) were generally not clinically meaningful and showed no apparent trends across the treatment groups. Velphoro had a similar GI adverse event profile [see Adverse Reactions (6.1)] to sevelamer hydrochloride, and no dose-dependent trend in GI events was observed.

14.2 Dose Titration Study

In Study-05A, 1,055 adult patients on hemodialysis (N=968) or peritoneal dialysis (N=87) with serum phosphorus ≥6 mg/dL following a 2-4 week phosphate binder washout period, were randomized and treated with either Velphoro, at a starting dose of 1,000 mg/day (N=707), or active-control (sevelamer carbonate, N=348) for 24 weeks. At the end of Week 24, 93 patients on hemodialysis whose serum phosphorus levels were controlled (<5.5 mg/dL) with Velphoro in the first part of the study, were re-randomized to continue treatment with either their Week 24 maintenance dose (N=44 or a non-effective low dose control 250 mg/day, N=49) of Velphoro for a further 3 weeks. At Week 27, a superiority analysis of the Velphoro maintenance dose versus low dose was performed. The maximum dose of Velphoro was 3,000 mg/day (6 tablets/day) and the minimum dose was 1,000 mg/day (2 tablets/day). Velphoro was administered with food and the daily dose was divided across the largest meals of the day.

The Velphoro maintenance dose (1,000 to 3,000 mg/day) was statistically significantly superior in sustaining the phosphorus lowering effect in hemodialysis patients at Week 27 (p<0.001) compared with the non-effective low dose control. The results are provided in Table 2.

Table 2 Mean (SD) Serum Phosphorus and Change from Baseline to End of Treatment
 | Mean (SD) Serum Phosphorus (mg/dL)
 | Velphoro Maintenance Dose (1,000 to 3,000 mg/day) (N=44) | Velphoro Low Dose Control (250 mg/day) (N=49)
Week 24 (BL) | 4.7 (1.03) | 5.0 (1.14)
Week 25 | 4.7 (0.91) | 6.3 (1.44)
Week 26 | 4.7 (1.21) | 6.6 (1.91)
Week 27/End of Treatment | 5.0 (1.07) | 6.8 (1.63)
Change from BL to End of Treatment | 0.3 (1.22)* | 1.8 (1.47)
* p<0.001 for the difference in least square means of the change from BL to Week 27/End of Treatment (LOCF principle) between Velphoro maintenance dose and low dose using a covariance analysis (MIXED Model).
Notes: BL is Week 24 or latest value available before Week 24 when Week 24 result is missing; End of Treatment is Week 27 value or includes the latest evaluable measurement after Week 24 (i.e., LOCF).
BL = Baseline; LOCF = Last observation carried forward; SD = Standard deviation.

Following completion of Study-05A, 658 patients (597 on hemodialysis and 61 on peritoneal dialysis) were treated in the 28-week extension study (Study-05B) with either Velphoro (N=391) or sevelamer carbonate (N=267) according to their original randomization.

Serum phosphorus levels declined rapidly during the first few weeks of treatment and remained relatively constant thereafter. The phosphorus lowering effect of Velphoro was consistently maintained and controlled through 12 months of treatment (shown in Figure 1). The proportion of adherent patients for Velphoro was 86% at 52 weeks.

Figure 1Mean change (±SEM) from baseline in serum phosphorus over time in Study‑05A and extension Study‑05B. Insert showing the mean change (±SEM) from baseline in serum phosphorus during the withdrawal phase of the study (Weeks 24 to 27) for Velphoro non-effective low dose control (250 mg/day) versus Velphoro maintenance dose.

Age, gender, race, or dialysis modality did not affect the efficacy of Velphoro.

There were no clinically meaningful changes for serum iron, ferritin, TSAT levels, vitamins (A, D, E and K) with Velphoro. There was no evidence of accumulation of iron during one year treatment.

14.3 Pediatric Study

A clinical study of Velphoro (NCT02688764) was conducted in pediatric patients with hyperphosphatemia and advanced CKD (defined as an estimated glomerular filtration rate <30 mL/min/l.73m^2or CKD on dialysis). Following a washout period of up to 3 weeks, 78 patients 6 to 18 years of age were randomized to Velphoro (N=60) or active control calcium acetate (Phoslyra) (N=18) for a 10-week dose titration period, followed by a 24-week safety extension. Approximately 81% of patients were CKD patients on dialysis (69% on hemodialysis and 12% on peritoneal dialysis). 43 patients randomized to Velphoro completed the dose titration period.

The least squares (LS) mean reduction in serum phosphorus levels from baseline to the end of the dose titration period in the Velphoro group (N=59) was -0.52 mg/dL (95% CI: -0.97, -0.07). The percentage of patients with serum phosphorus levels within normal ranges increased from 39% at baseline to 64% at the end of the dose titration period.

Velphoro is not approved in pediatric patients 6 years to less than 9 years of age because of the lack of an appropriate dosage strength.

The median prescribed daily dose of Velphoro was approximately 1500 mg during the dose titration period for patients 9 to 18 years of age.

16 HOW SUPPLIED/STORAGE AND HANDLING

16.1 How Supplied

Velphoro chewable tablets are brown, circular, bi-planar tablets, embossed with “PA 500” on 1 side. Each tablet of Velphoro contains 500 mg iron as sucroferric oxyhydroxide. Velphoro tablets are packaged as follows:

NDC 49230-645-51 Bottle of 90 tablets

16.2 Storage

Keep the bottle tightly closed in order to protect from moisture.

Store at 25°C (77°F) with excursions permitted to 15°C to 30°C (59°F to 86°F).

[See USP Controlled Room Temperature]

17 PATIENT COUNSELING INFORMATION

Inform patients that Velphoro tablets should be chewed or crushed. Do not swallow whole [see Dosage and Administration (2.2)].

Advise patients that Velphoro should be taken with meals.

Instruct patients on concomitant medications that should be dosed apart from Velphoro [see Drug Interactions (7)].

Inform patients that Velphoro can cause discolored (black) stool, but this discoloration of the stool is considered normal with oral medications containing iron.

Inform patients that Velphoro can stain teeth.

Inform patients to report any rash to their health care professional.

Distributed by:
Fresenius Medical Care North America
920 Winter Street
Waltham, MA 02451
Patents Apply – visit www.fmcna.com/patents

© 2014-2020, Fresenius Medical Care North America. All Rights Reserved.

PACKAGE LABEL

Principal Display Label - Bottle Label - NDC 49230-645-51

PACKAGE LABEL

Principal Display Label - Bottle Carton - NDC 49230-645-51